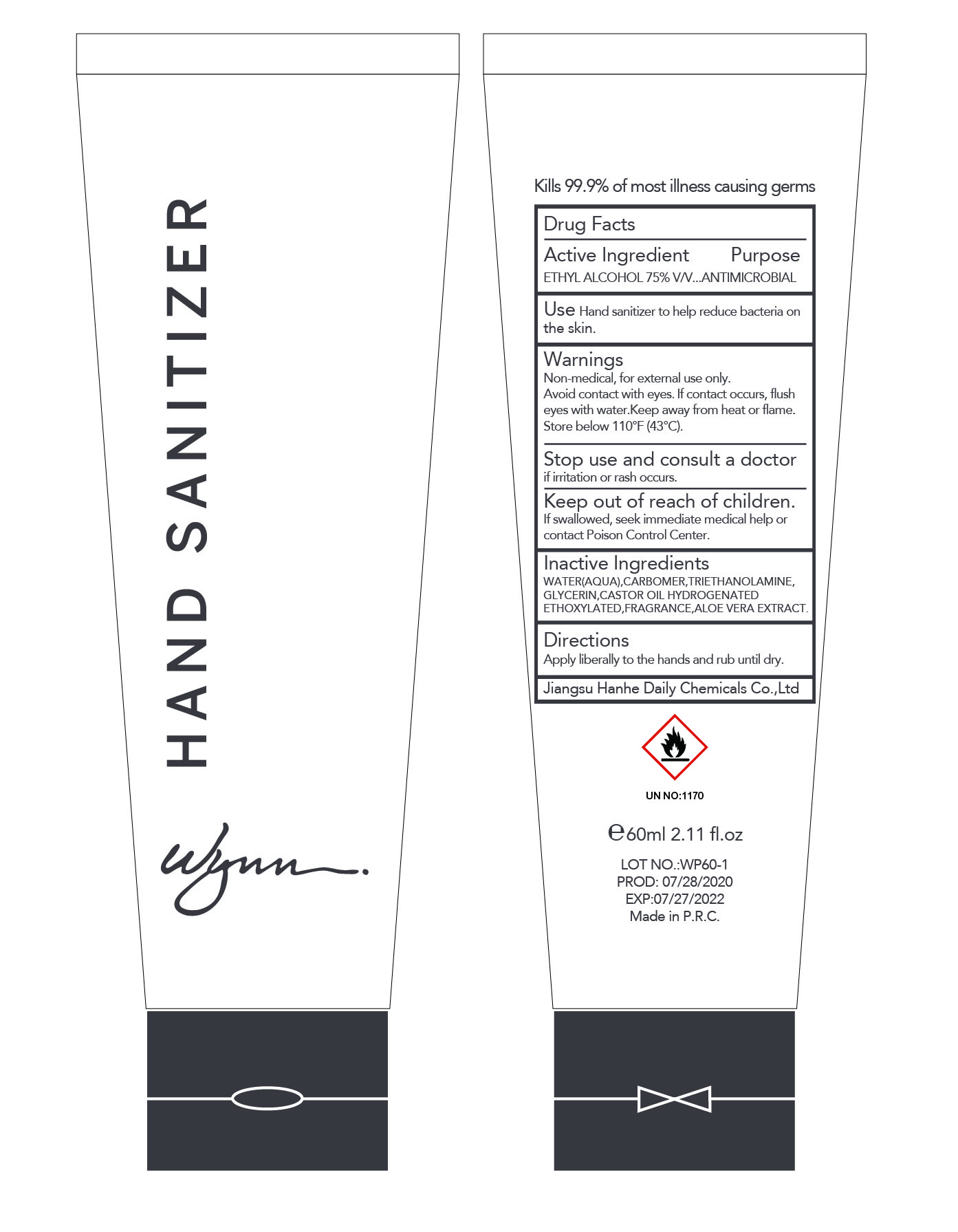 DRUG LABEL: Wynn Hand Sanitizer
NDC: 73027-210 | Form: SOLUTION
Manufacturer: JIANGSU HANHE DAILY CHEMICALS CO., LTD.
Category: otc | Type: HUMAN OTC DRUG LABEL
Date: 20211102

ACTIVE INGREDIENTS: ALCOHOL 75 mL/100 mL
INACTIVE INGREDIENTS: CARBOMER 940; TROLAMINE; GLYCERIN; ALOE VERA LEAF

73027-210

ACTIVE INGREDIENT

Ethyl Alcohol 75% v/v

Purpose

Antimicrobial

Use

Hand sanitizer to help reduce bacteria on the skin

Warnings

Non Medical, For external use only.

Flammable. Keep away from heat or flame

Avoid contact with eyes. If contact occurs, flush eyes with water

Store below 110F (43C)

Stop use and consult a doctor if irritation or rash occurs.

Keep out of reach of children. If swallowed, seek immediate medical help or contact a poison control center

Directions

- Apply literally to the hands and rub until dry

Inactive ingredients

Water, Carbomer, Triethanolamine, Glycerin, Castor Oil Hydrogenated Ethoxylated, Fragrance, Aloe Vera Extract